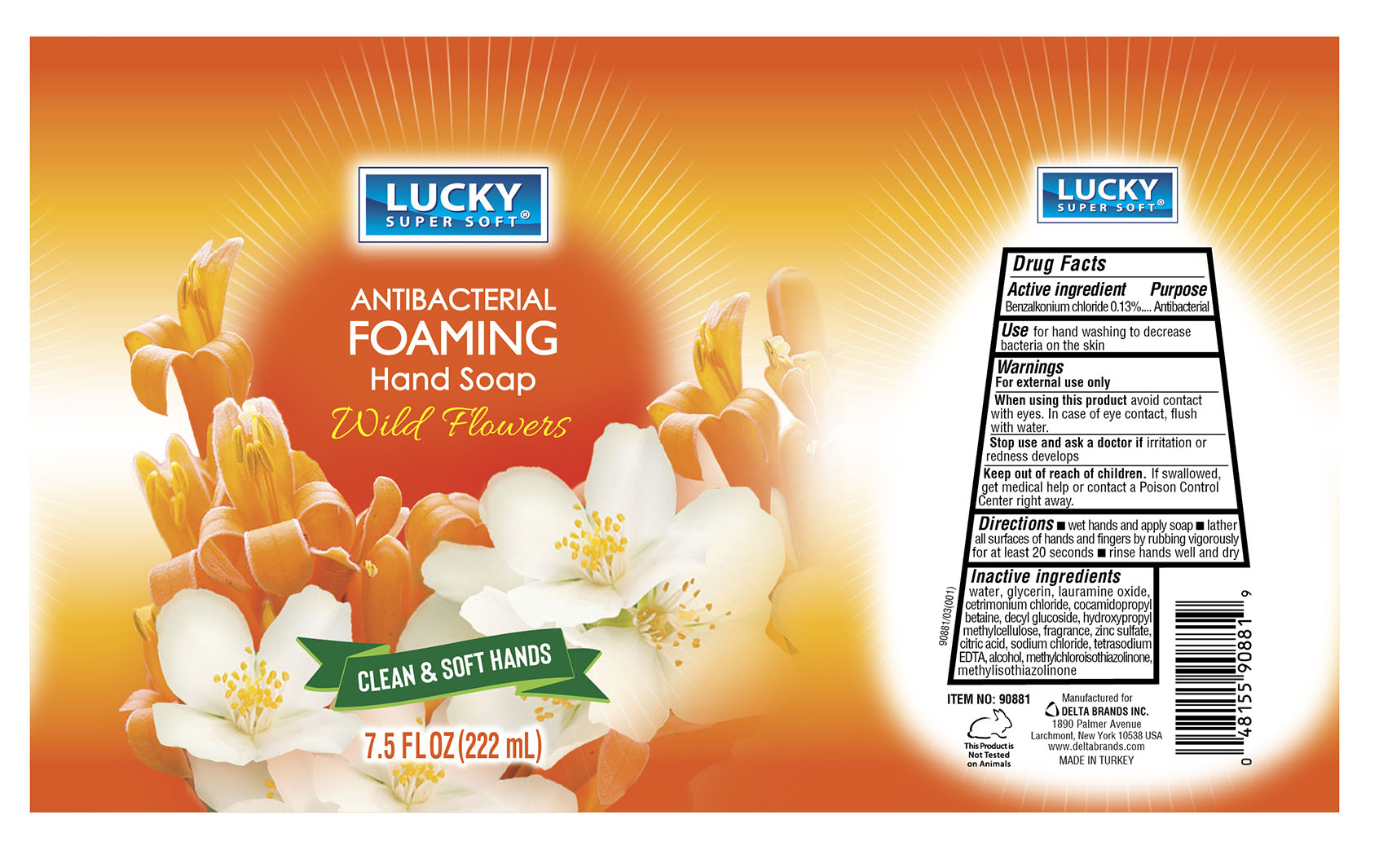 DRUG LABEL: LUCKY SUPER SOFT
NDC: 20276-138 | Form: SOAP
Manufacturer: Delta Brands, Inc
Category: otc | Type: HUMAN OTC DRUG LABEL
Date: 20230622

ACTIVE INGREDIENTS: BENZALKONIUM CHLORIDE 0.13 g/100 mL
INACTIVE INGREDIENTS: WATER; DECYL GLUCOSIDE; LAURAMINE OXIDE; GLYCERIN; CETRIMONIUM CHLORIDE; COCAMIDOPROPYL BETAINE; HYPROMELLOSE, UNSPECIFIED; ZINC SULFATE; METHYLCHLOROISOTHIAZOLINONE; METHYLISOTHIAZOLINONE; EDETATE SODIUM; CITRIC ACID MONOHYDRATE; SODIUM CHLORIDE; ALCOHOL

LckyHandSoapWldFlwrsBZK013

Active ingredient

Benzalkonium Chloride 0.13%

Purpose

Antibacterial

Use

for hand washing to decrease bacteria on the skin

Warnings

For external use only

When using this product

avoid contact with the eyes. In case of eye contact, flush with water.

Stop use and ask a doctor if

irritation and redness develops

Keep out of reach of children

If swallowed, get medical help or contact a Poison Control Center right away.

Directions

■ wet hands and apply soap ■ lather all surfaces of hands and fingers by rubbing vigorously for at least 20 seconds ■ rinse hands well and dry

Inactive ingredients

water, glycerin, lauramine oxide, cetrimonium chloride, cocamidopropyl betaine, decyl glucoside, hydroxypropyl methylcellulose, fragrance, zinc sulfate, citric acid, sodium chloride, tetrasodium EDTA, alcohol, methylchloroisothiazolinone, methylisothiazolinone